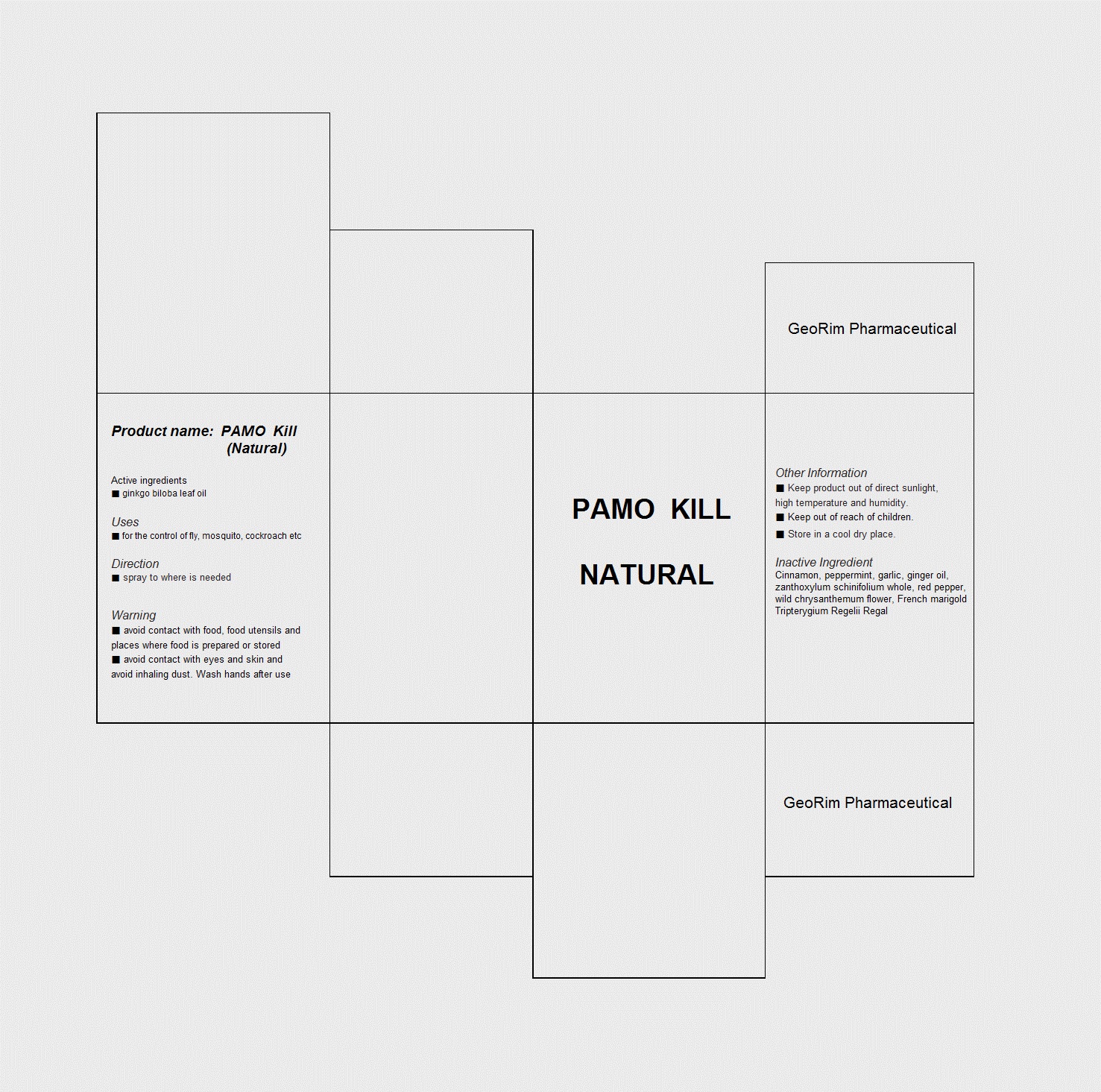 DRUG LABEL: PAMO Kill Natural
NDC: 59494-1001 | Form: LIQUID
Manufacturer: GeoRim Pharmaceutical
Category: otc | Type: HUMAN OTC DRUG LABEL
Date: 20130902

ACTIVE INGREDIENTS: GINKGO BILOBA LEAF OIL 1 g/100 mL
INACTIVE INGREDIENTS: CINNAMON; PEPPERMINT; GARLIC OIL; GINGER OIL; ZANTHOXYLUM SCHINIFOLIUM WHOLE; RED PEPPER; DENDRANTHEMA INDICUM FLOWER

Drug Facts

ACTIVE INGREDIENT

ginkgo biloba leaf oil

INACTIVE INGREDIENT

cinnamon, peppermint, garlic, ginger oil, zanthoxylum schinifolium whole, red pepper, wild chrysanthemum flower, french marigold, tripterygium regelii regal

PURPOSE

for the control of fly, mosquito cockroach etc

keep out or reach of the children

INDICATIONS AND USAGE

spray to where is needed

WARNINGS

avoid contact with food, food, utensils and places where food is prepared or stored
avoid contact with eyes and skin and avoid inhaling dust. wash hands after use

DOSAGE AND ADMINISTRATION

for external use only